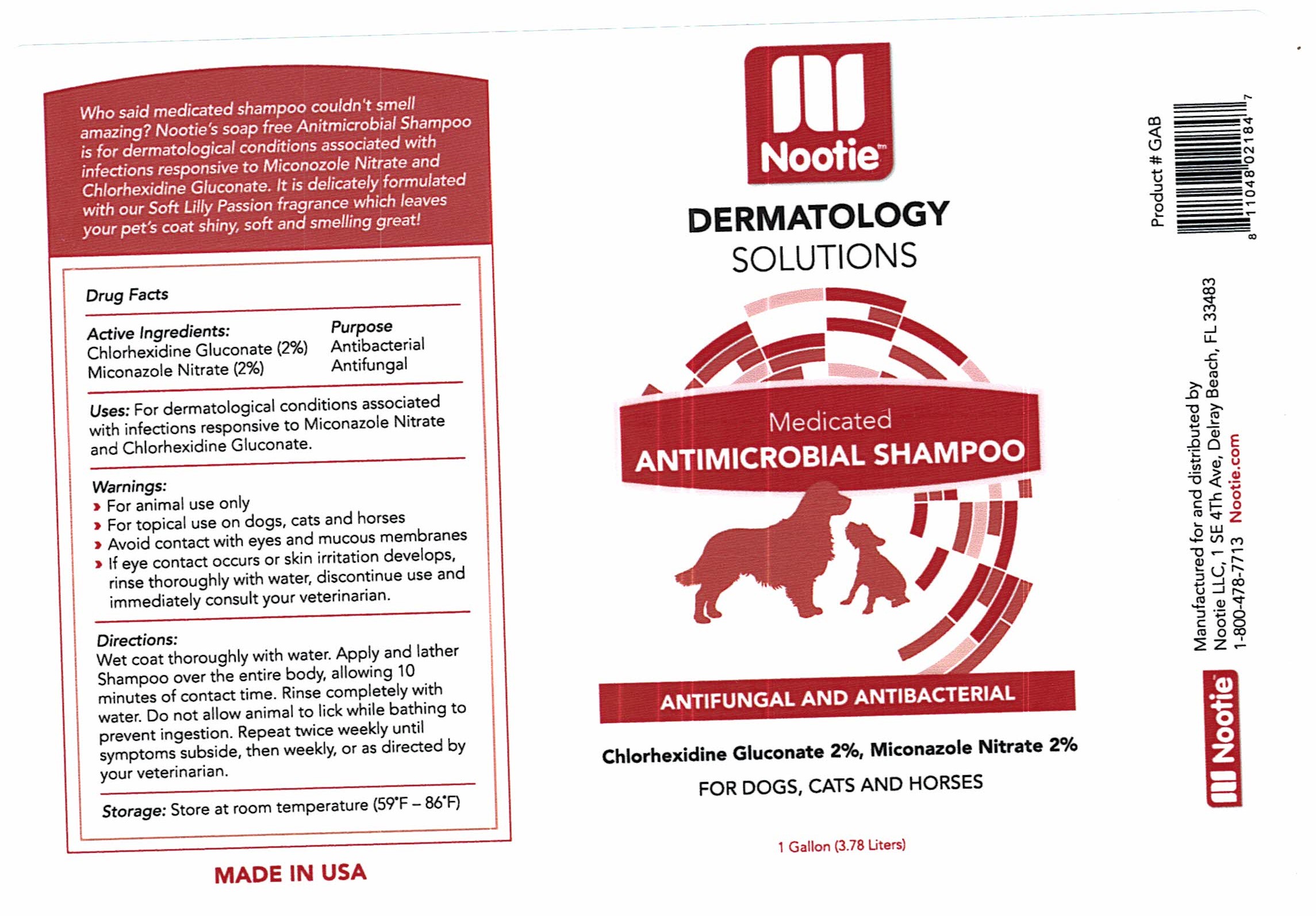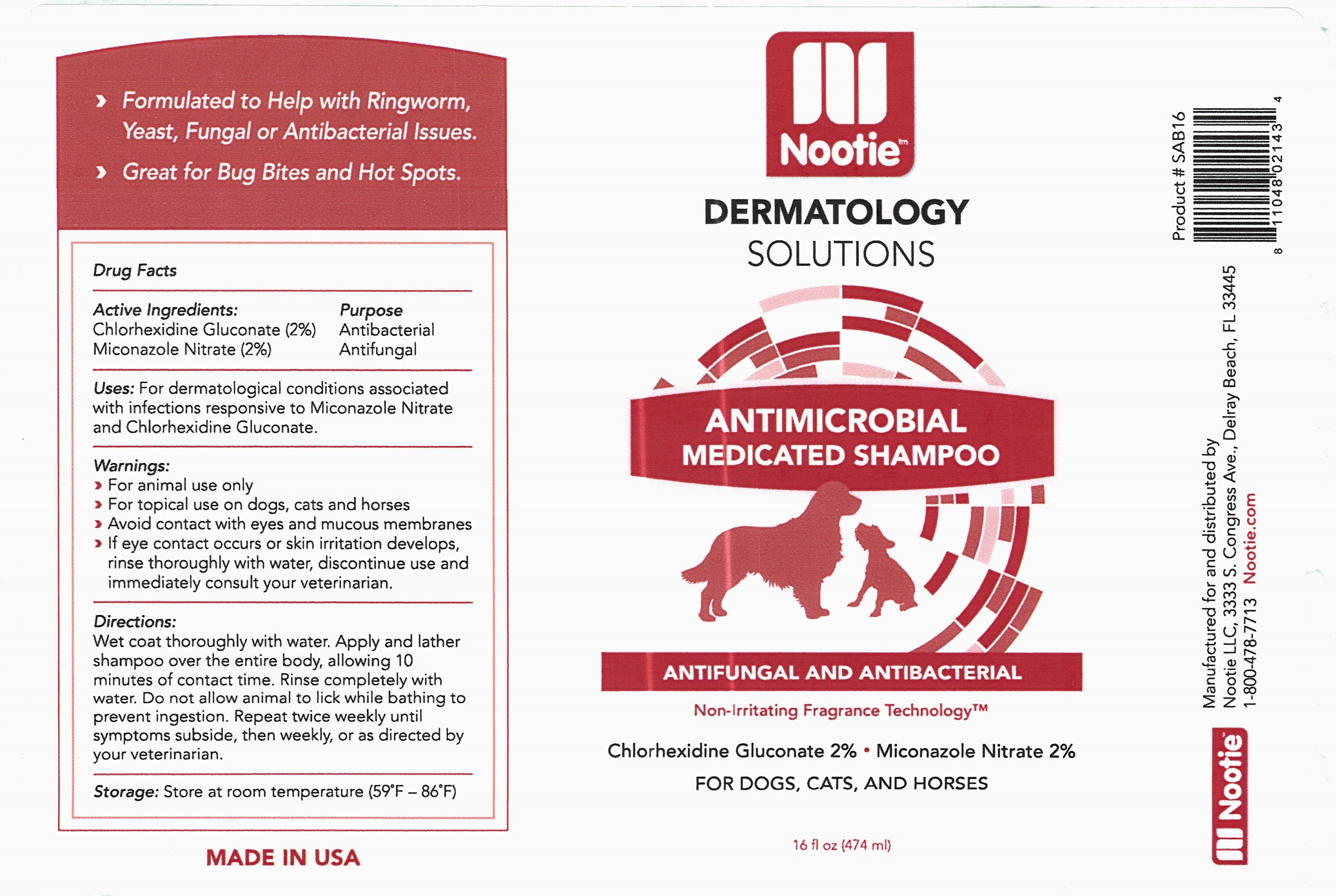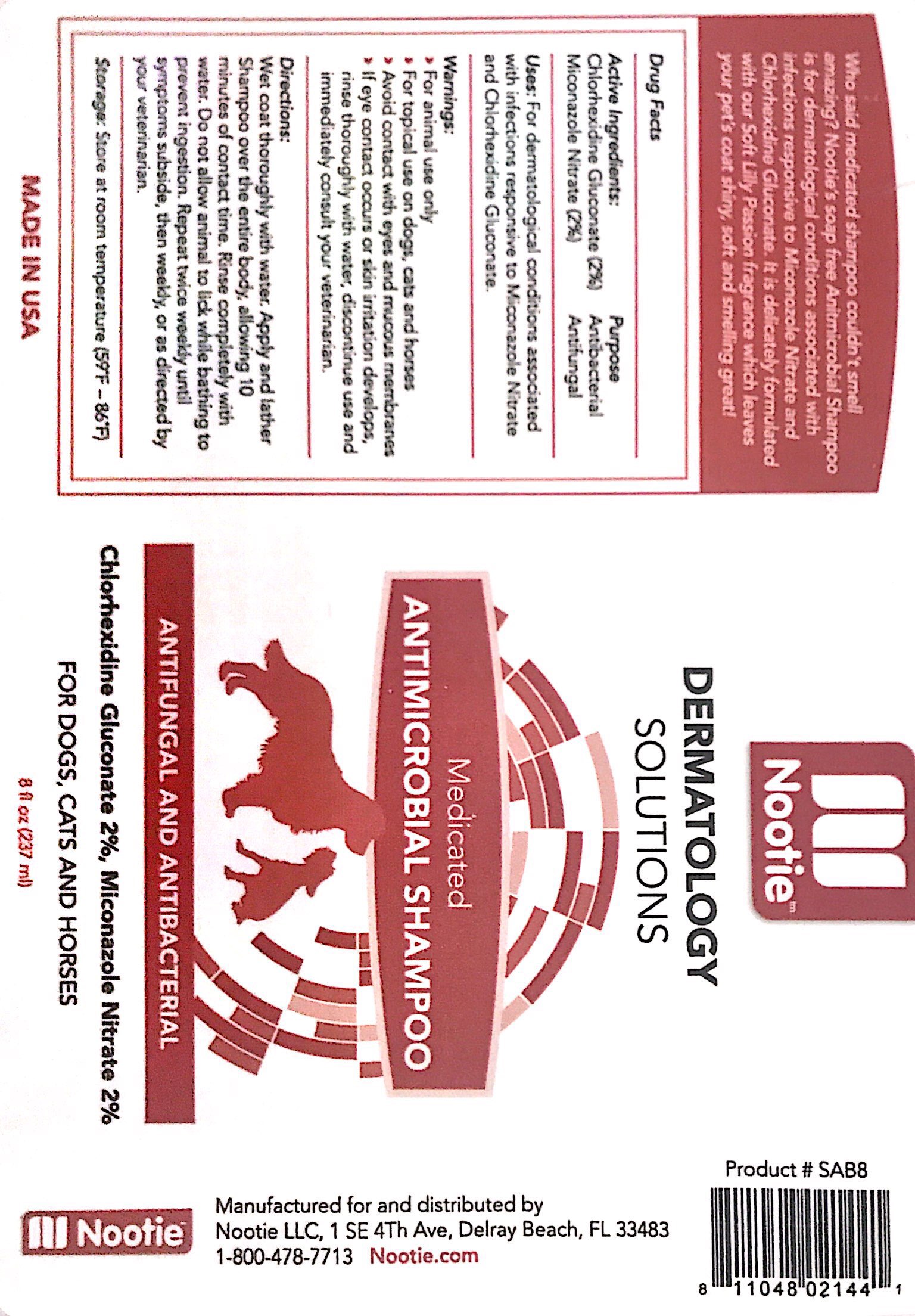 DRUG LABEL: Medicated Antimicrobial
NDC: 51437-203 | Form: SHAMPOO
Manufacturer: Nootie, LLC
Category: animal | Type: OTC ANIMAL DRUG LABEL
Date: 20211111

ACTIVE INGREDIENTS: CHLORHEXIDINE GLUCONATE 2 g/100 mL; MICONAZOLE NITRATE 2 g/100 mL

Dermatology Solutions Medicated Antimicrobial Shampoo (51437-203)

Drug Facts

Active Ingredients: Purpose
Chlorhexidine Gluconate (2%) Antibacterial
Miconazole Nitrate (2%) Antifungal

INDICATIONS AND USAGE

Uses: For dermatological conditions associated with infections responsive to Miconazole Nitrate and Chlorhexidine Gluconate.

Directions:

Wet coat thoroughly with water. Apply and lather Shampoo over the entire body, allowing 10 minutes of contact time. Rinse completely with water. Do not allow animal to lick while bathing to prevent ingestion. Repeat twice weekly until symptoms subside, then weekly, or as directed by your veterinarian.

Warnings:

- For animal use only
- For topical use on dogs, cats and horses
- Avoid contact with eyes and mucous membranes
- If eye contact occurs or skin irritation develops, rinse thoroughly with water, discontinue use and immediately consult your veterinarian.

Storage: Store at room temperature (59°F-86°)

MADE IN USA

PACKAGE LABEL

Nootie

DERMATOLOGY

SOLUTIONS

Medicated

ANTIMICROBIAL SHAMPOO

ANTIFUNGAL AND ANTIBACTERIAL

Chlorhexidine Gluconate 2%, Miconazole Nitrate 2%

FOR DOGS, CATS AND HORSES

8 fl oz (237ml) / 16 fl oz (474 ml) / 1 Gallon (3785 ml)

Nootie
Manufactured for and distributed by
Nootie LLC, 1 SE 4th Ave, Delray Beach, FL 33483
1-800-478-7713 Nootie.com
Product # SAB8 / # SAB16/ # GAB